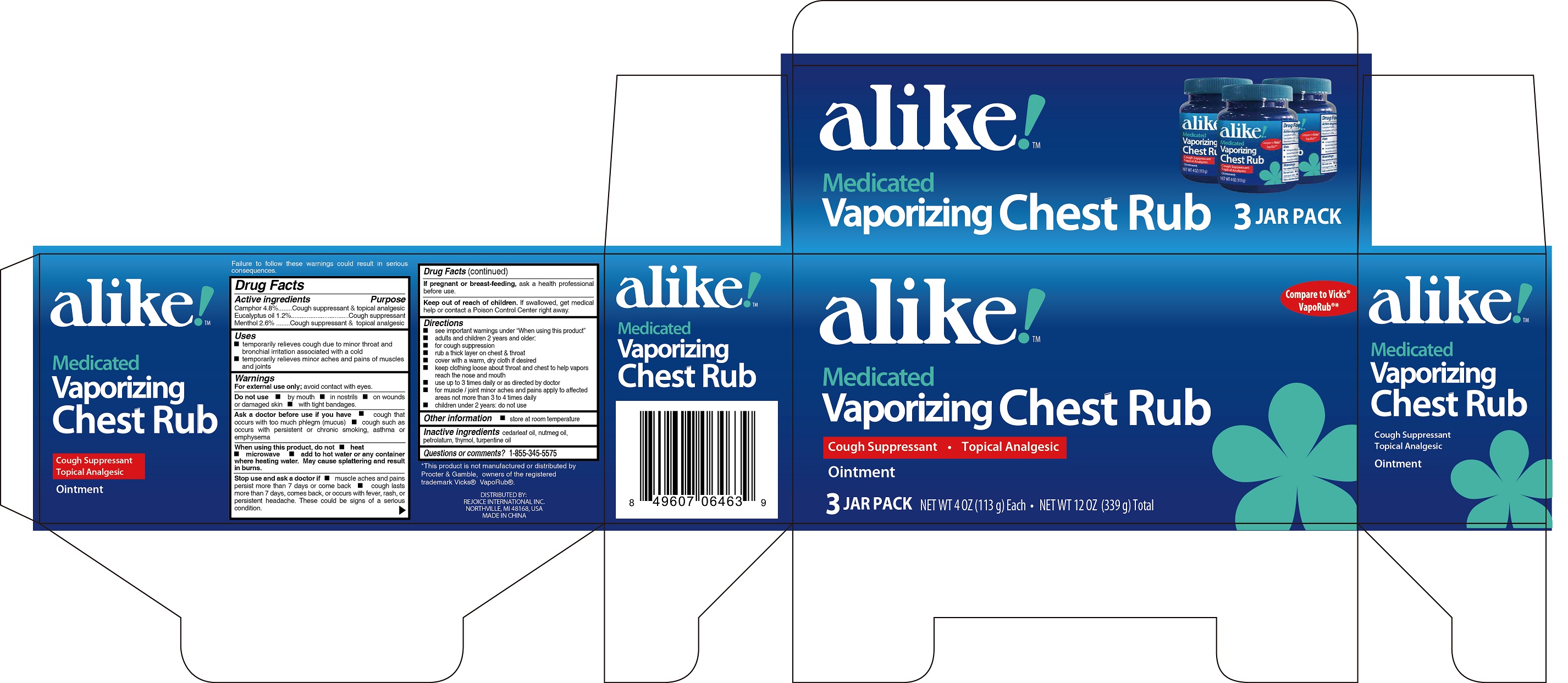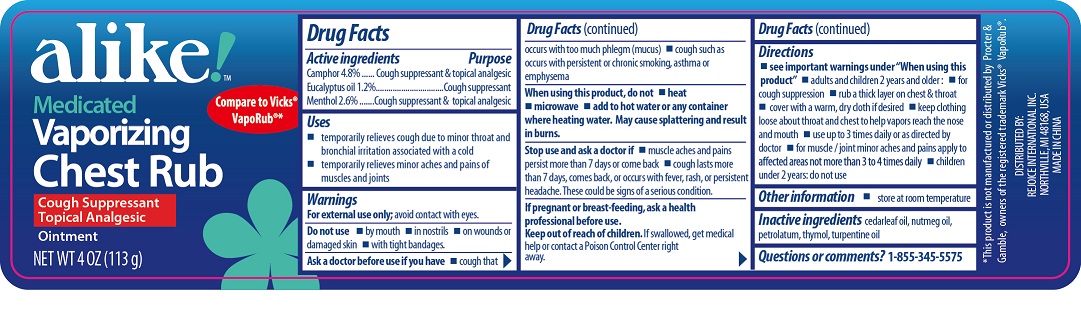 DRUG LABEL: Vaporizing Chest Rub 4 oz.
NDC: 57337-099 | Form: OINTMENT
Manufacturer: Rejoice International Inc.
Category: otc | Type: HUMAN OTC DRUG LABEL
Date: 20250212

ACTIVE INGREDIENTS: CAMPHOR (NATURAL) 4.8 g/100 mL; EUCALYPTUS OIL 1.2 g/100 mL; MENTHOL 2.6 g/100 mL
INACTIVE INGREDIENTS: CEDAR LEAF OIL; NUTMEG OIL; PETROLATUM; THYMOL; TURPENTINE OIL

Vaporizing Chest Rub 4 oz 3 pk

Active ingredients

Camphor, 4.8%

Eucalyptus Oil, 1.2%

Menthol, 2.6%

Purpose

Cough suppressant & topical analgesic

Keep out of reach of children. If swallowed, get medical help or contact a Poison Control Center right away.

Uses

- temporarily relieves cough due to minor throat and bronchial irritation associated with a cold.
- temporarily relieves minor aches and pains of muscles and joints

Warnings

For external use only; avoid contact with eyes

Do not use

- by mouth
- in nostrils
- on wounds or damaged skin
- with tight bandages

Ask a doctor before use if you have

- cough that occurs with too much phlegm (mucus)
- cough such as occurs with persistent of chronic smoking, asthma or emphysema

When using this product, do not

- heat
- microwave
- add to hot water or any container where heating water. May cause spattering and result in burns.

Stop use and ask a doctor if

- muscles aches and pains persist more than 7 days or come back
- cough lasts more than 7 days, comes back, or occurs with fever, rash, or persistent headche. These could be signs of a serious condition.

Directions

- See important warnings under "When using this product"
- adults and children 2 years and older

For cough suppression

- rub a thick layer on chest & throat
- cover with a warm, dry cloth if desired
- keep clothing loose and throat and chest to help vapors reach the nose and mouth
- use up to 3 times daily or as directed as doctor
- for muscle / joint minor aches and pains apply to affected areas not more than 3 to 4 times daily
- children under 2 years; do not use

Inactive ingredients

Cedarleaf Oil, Nutmeg Oil, Petrolatum, Thymol, Turpentine Oil